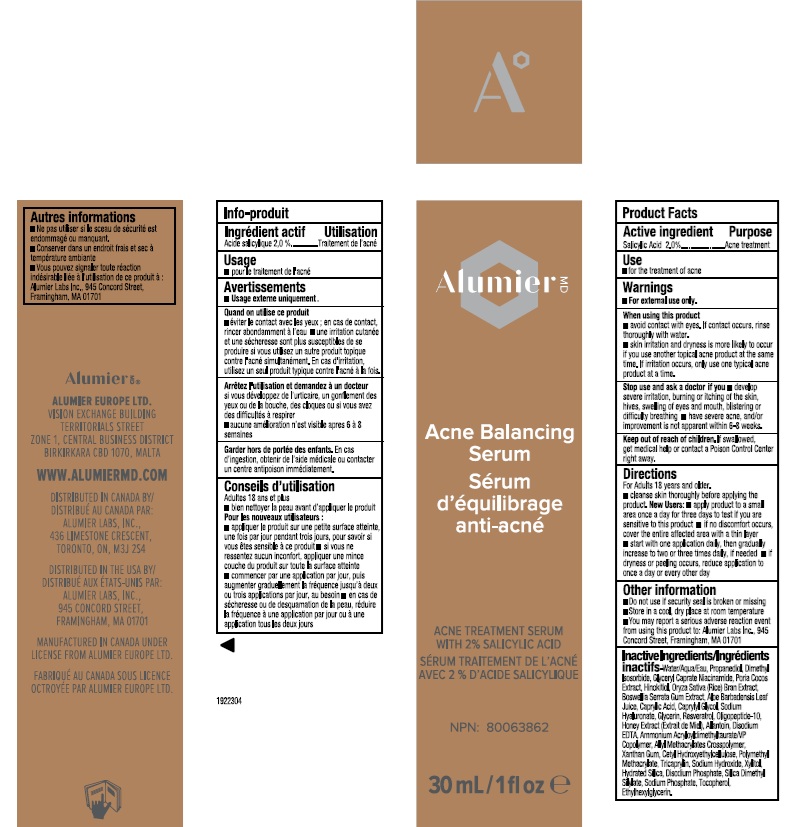 DRUG LABEL: Alumier MD Acne Balancing Serum
NDC: 69473-002 | Form: CREAM
Manufacturer: Alumier Labs
Category: otc | Type: HUMAN OTC DRUG LABEL
Date: 20250806

ACTIVE INGREDIENTS: SALICYLIC ACID 20 mg/1 mL
INACTIVE INGREDIENTS: ALLANTOIN; ALOE VERA LEAF; CAPRYLIC ACID; EDETATE DISODIUM; HYALURONATE SODIUM; RESVERATROL; XANTHAN GUM; TRICAPRYLIN; XYLITOL; PROPANEDIOL; WATER; DIMETHYL ISOSORBIDE; INDIAN FRANKINCENSE; CAPRYLYL GLYCOL; OLIGOPEPTIDE-10; HONEY; GLYCERIN; AMMONIUM ACRYLOYLDIMETHYLTAURATE/VP COPOLYMER; POLY(METHYL METHACRYLATE; 450000 MW); SODIUM PHOSPHATE; RICE BRAN; NIACINAMIDE; GLYCERYL CAPRATE; TOCOPHEROL; SODIUM HYDROXIDE; ETHYLHEXYLGLYCERIN; .BETA.-THUJAPLICIN; FU LING; HYDRATED SILICA; DISODIUM PHOSPHATE; CETYL HYDROXYETHYLCELLULOSE (350000 MW); SILICA DIMETHYL SILYLATE

Alumier MD Acne Balancing Serum

Active ingredient

Salicylic Acid 2.0%

Purpose

Acne treatment

Use

- for the treatment of acne

Warnings

- For external use only.

When using this product

- avoid contact with eyes. If contact occurs, rinse thoroughly with water.
- skin irritation and dryness is more likely to occur if you use another topical acne product at the same time. If irritation occurs, only use one topical acne product at a time.

Stop use and ask a doctor if you

- develop severe irritation, burning or itching of the skin, hives, swelling of eyes and mouth, blistering or difficulty breathing
- have severe acne, and/or iimprovement is not apparent within 6-8 weeks

Keep out of reach of children. If swallowed, get medical help or contact a Poison Control Center right away.

Directions

For Adults 18 years and older

- cleanse skin thoroughly before applying the product

New Users:

- apply product to a small area once a day for three days to test if you are sensitive to this product
- if no discomfort occurs, cover the entire affected area with a thin layer
- start with one application daily, then gradually increase to two to three times daily, if needed
- if dryness or peeling occurs, reduce application to once a day or every other day

Other information

- Do not use if security seal is broken or missing
- Store in a cool, dry place at room temperature
- You may report a serious adverse reaction event from using this product to: Alumier Labs Inc., 945 Concord Street, Framingham, MA 01701

Inactive Ingredients

Water/Aqua/Eau, Propanediol, Dimethyl Isosorbide, Glyceryl Caprate, Niacinamide, Poria Cocos Extract, Hinokitiol, Oryza Sativa (Rice) Bran Extract, Boswellia Serrata Gum Extract, Aloe Barbadensis Leaf Juice, Caprylic Acid, Caprylyl Glycol, Sodium Hyaluronate, Glycerin, Resveratrol, Oligopeptide-10, Honey Extract (Extrait de Miel), Allantoin, Disodium EDTA, Ammonium Acryloyldimethyltaurate/VP Copolymer, Allyl Methacrylates Crosspolymer, Xanthan Gum, Cetyl Hydroxyethylcellulose, Polymethyl Methacrylate, Tricaprylin, Sodium Hydroxide, Xylitol, Hydrated Silica, Disodium Phosphate, Silica Dimethyl Silylate, Sodium Phosphate, Tocopherol, Ethylhexylglycerin.